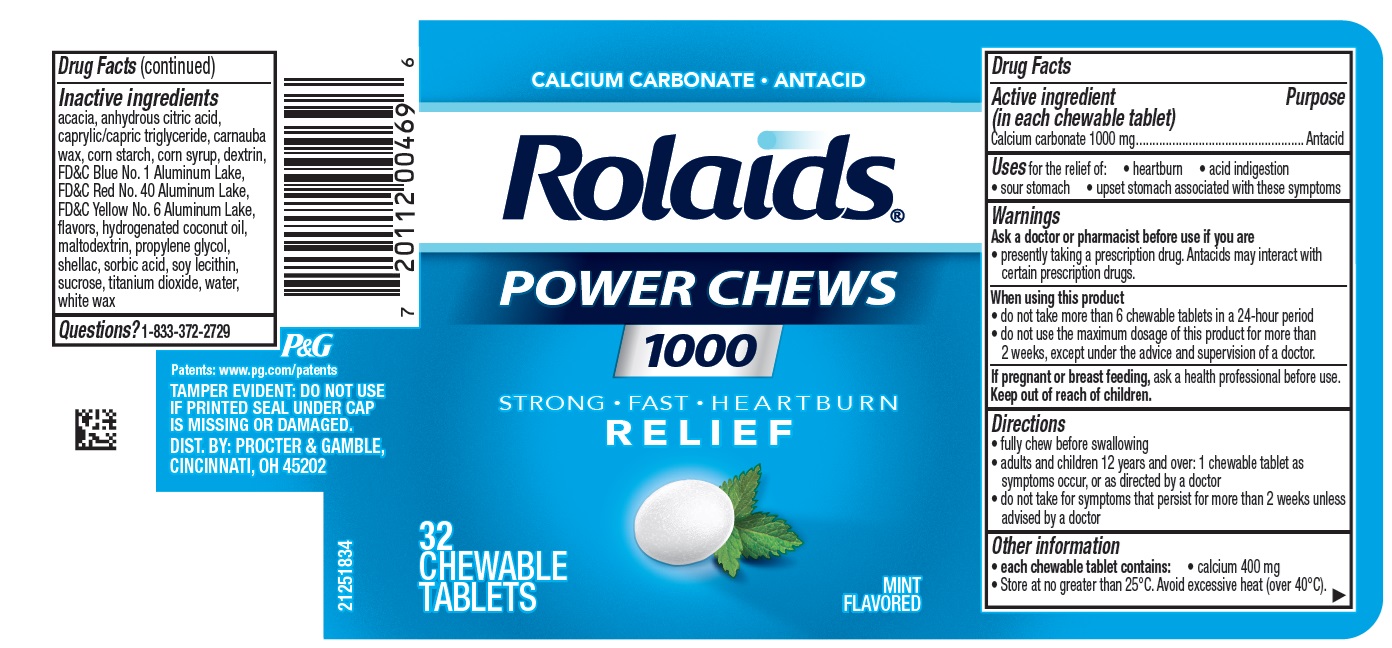 DRUG LABEL: Rolaids
NDC: 84126-348 | Form: TABLET, CHEWABLE
Manufacturer: The Procter & Gamble Manufacturing Company
Category: otc | Type: HUMAN OTC DRUG LABEL
Date: 20250304

ACTIVE INGREDIENTS: CALCIUM CARBONATE 1000 mg/1 1
INACTIVE INGREDIENTS: STARCH, CORN; CORN SYRUP; HYDROGENATED COCONUT OIL; SUCROSE; WATER; ACACIA; ANHYDROUS CITRIC ACID; CAPRYLIC/CAPRIC TRIGLYCERIDE; CARNAUBA WAX; ICODEXTRIN; FD&C BLUE NO. 1 ALUMINUM LAKE; FD&C RED NO. 40 ALUMINUM LAKE; FD&C YELLOW NO. 6 ALUMINUM LAKE; MALTODEXTRIN; PROPYLENE GLYCOL; SHELLAC; SORBIC ACID; SOYBEAN LECITHIN; TITANIUM DIOXIDE; WHITE WAX

Rolaids® POWER CHEWS 1000

Drug Facts

Active ingredient (in each chewable tablet)

Calcium carbonate 1000 mg

Purpose

Antacid

Uses

for the relief of: • heartburn • acid indigestion • sour stomach • upset stomach associated with these symptoms

Warnings

Ask a doctor or pharmacist before use if you are

• presently taking a prescription drug. Antacids may interact with certain prescription drugs.

When using this product

- do not take more than 6 chewable tablets in a 24-period
- do not use the maximum dosage of this product for more than 2 weeks, except under the advice and supervision of a doctor.

If pregnant or breast feeding,

ask a health professional before use.

Directions

- fully chew before swallowing
- adults and children 12 years and over: 1 chewable tablet as symptoms occur, or as directed by a doctor
- do not take for symptoms that persist for more than 2 weeks unless advised by a doctor

Other information

- each chewable tablet contains: calcium 400 mg
- store at no greater than 25°C. Avoid excessive heat (over 40°C).

Inactive ingredients

acacia, anhydrous citric acid, caprylic/capric triglyceride, carnauba wax, corn starch, corn syrup, dextrin, FD&C Blue No. 1 Aluminum Lake, FD&C Red No. 40 Aluminum Lake, FD&C Yellow No. 6 Aluminum Lake, flavors, hydrogenated coconut oil, maltodextrin, propylene glycol, shellac, sorbic acid, soy lecithin, sucrose, titanium dioxide, water, white wax

Questions?

Call
1-833-372-2729

TAMPER EVIDENT: DO NOT USE IF PRINTED SEAL UNDER CAP IS MISSING OR DAMAGED.

DIST. BY PROCTER & GAMBLE,

CINCINNATI, OH 45202

PRINCIPAL DISPLAY PANEL

CALCIUM CARBONATE • ANTACID

Rolaids®POWER CHEWS

1000

STRONG • FAST • HEARTBURN RELIEF

32 CHEWABLE TABLETS

MINT FLAVORED